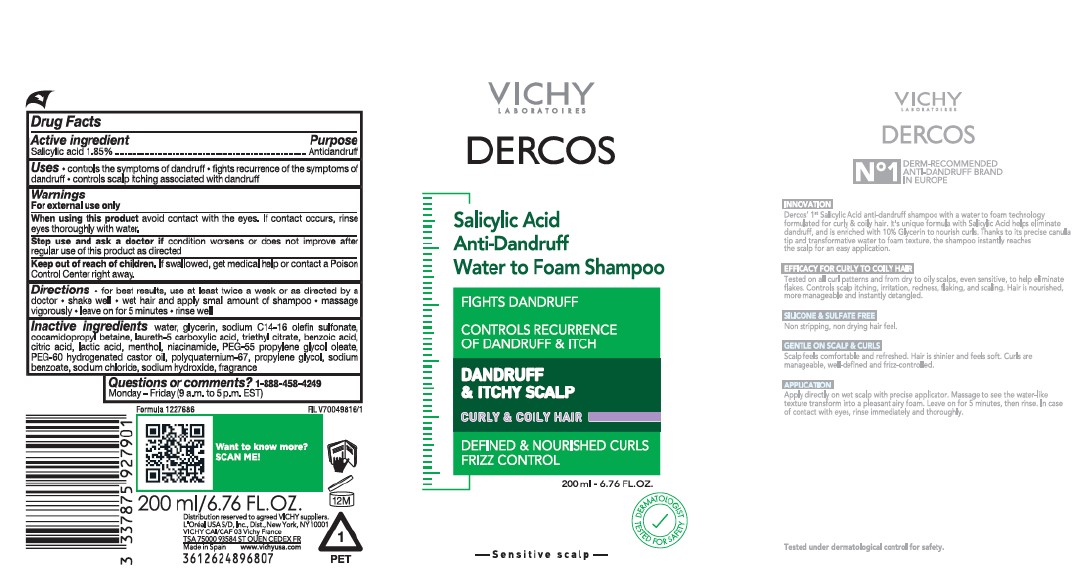 DRUG LABEL: Vichy Laboratoires Dercos Salicylic Acid Antidandruff Water to Foam
NDC: 49967-927 | Form: SHAMPOO
Manufacturer: L'Oreal USA Products Inc
Category: otc | Type: HUMAN OTC DRUG LABEL
Date: 20250604

ACTIVE INGREDIENTS: SALICYLIC ACID 18.5 mg/1 mL
INACTIVE INGREDIENTS: WATER; GLYCERIN; SODIUM C14-16 OLEFIN SULFONATE; COCAMIDOPROPYL BETAINE; LAURETH-5 CARBOXYLIC ACID; TRIETHYL CITRATE; BENZOIC ACID; CITRIC ACID; LACTIC ACID; MENTHOL; NIACINAMIDE; PEG-55 PROPYLENE GLYCOL OLEATE; PEG-60 HYDROGENATED CASTOR OIL; POLYQUATERNIUM-67 (400 CPS; 2.0-2.2 N%); PROPYLENE GLYCOL; SODIUM BENZOATE; SODIUM CHLORIDE; SODIUM HYDROXIDE

Drug Facts

Active ingredient

Salicylic acid 1.85%

Purpose

Antidandruff

Uses

- controls the symptoms of dandruff
- fights recurrence of the symptoms of dandruff
- controls scalp itching associated with dandruff

Warnings

For external use only

When using this product

Avoid contact with the eyes. If contact occurs, rinse eyes thoroughly with water.

Stop use and ask a doctor if

condition worsens or does not improve after regular use of this product as directed

Keep out of reach of children.

If swallowed, get medical help or contact a Poison Control Center right away.

Directions

- for best results, use at least twice a week or as directed by a doctor
- shake well
- wet hair and apply small amount of shampoo
- massage vigorously
- leave on for 5 minutes
- rinse well

Inactive ingredients

water, glycerin, sodium C14-16 olefin sulfonate, cocamidopropyl betaine, laureth-5 carboxylic acid, triethyl citrate, benzoic acid, citric acid, lactic acid, menthol, niacinamide, PEG-55 propylene glycol oleate, PEG-60 hydrogenated castor oil, polyquaternium-67, propylene glycol, sodium benzoate, sodium chloride, sodium hydroxide, fragrance

Questions or comments?

1-888-458-4249

Monday-Friday (9 a.m. - 5 p.m. EST)